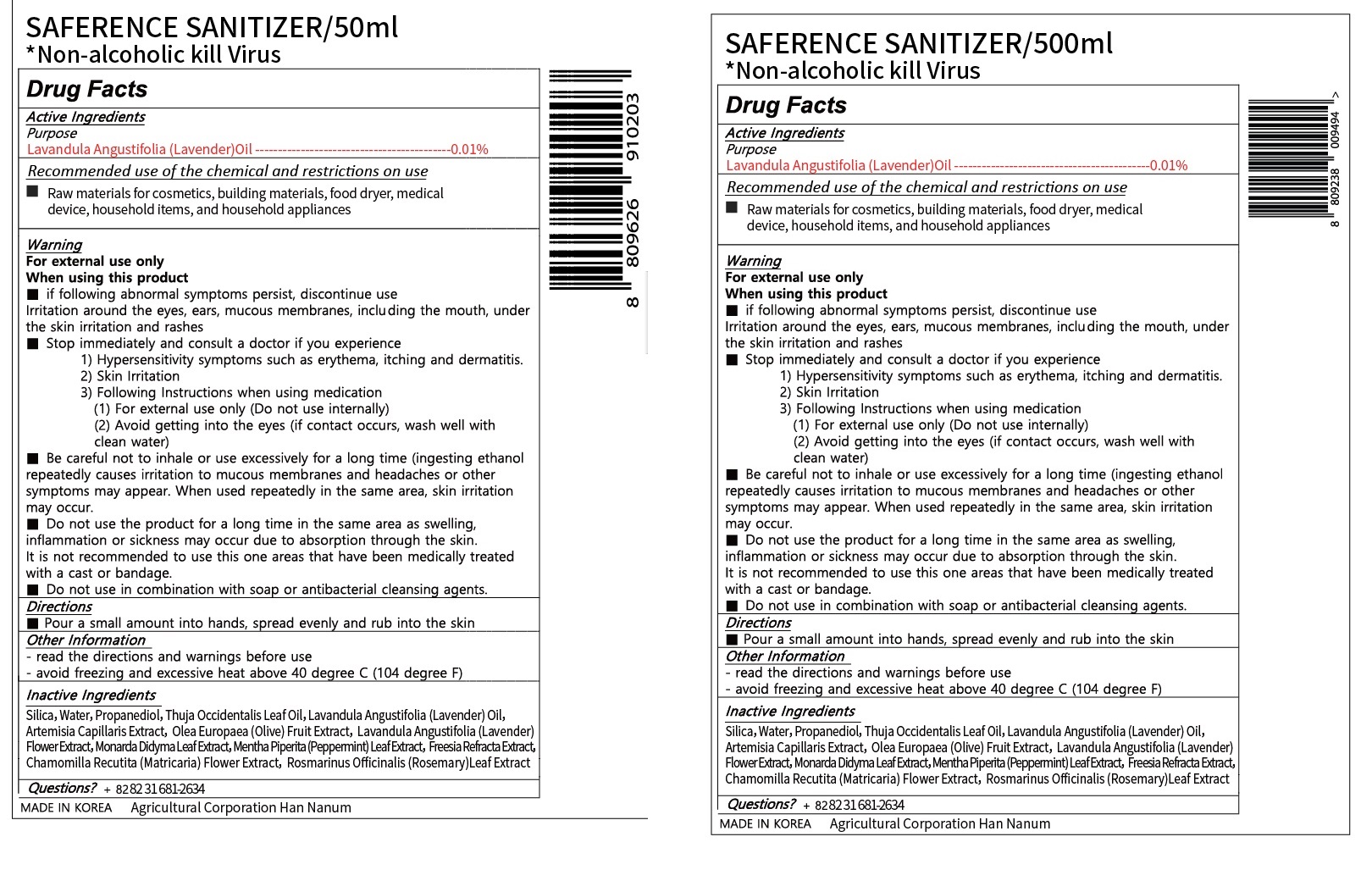 DRUG LABEL: SAFERENCE SANITIZER
NDC: 75693-0001 | Form: LIQUID
Manufacturer: MAY MEDIC CO LTD
Category: otc | Type: HUMAN OTC DRUG LABEL
Date: 20200424

ACTIVE INGREDIENTS: LAVENDER OIL 0.01 g/100 mL
INACTIVE INGREDIENTS: OLIVE OIL; WATER; PEPPERMINT OIL; PROPANEDIOL

Drug Facts

ACTIVE INGREDIENT

lavender oil

PURPOSE

see attached Drug Facts label

KEEP OUT OF REACH OF THE CHILDREN

WARNINGS

see attached Drug Facts label

DOSAGE AND ADMINISTRATION

for external use only

INACTIVE INGREDIENT

silia, water, propanediol, olive oil, etc (see attached Drug Facts label)

INDICATIONS AND USAGE

pour small amount into hands, spread evenly and rub into the skin